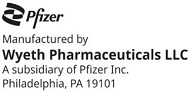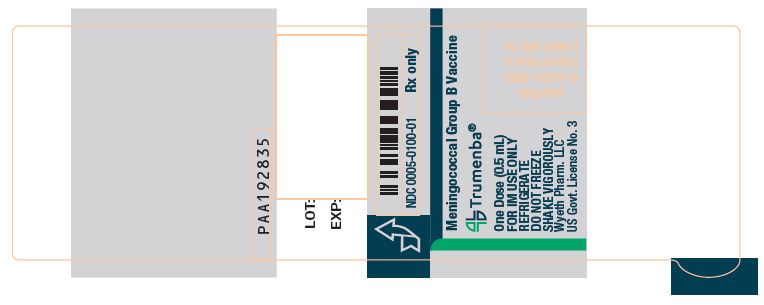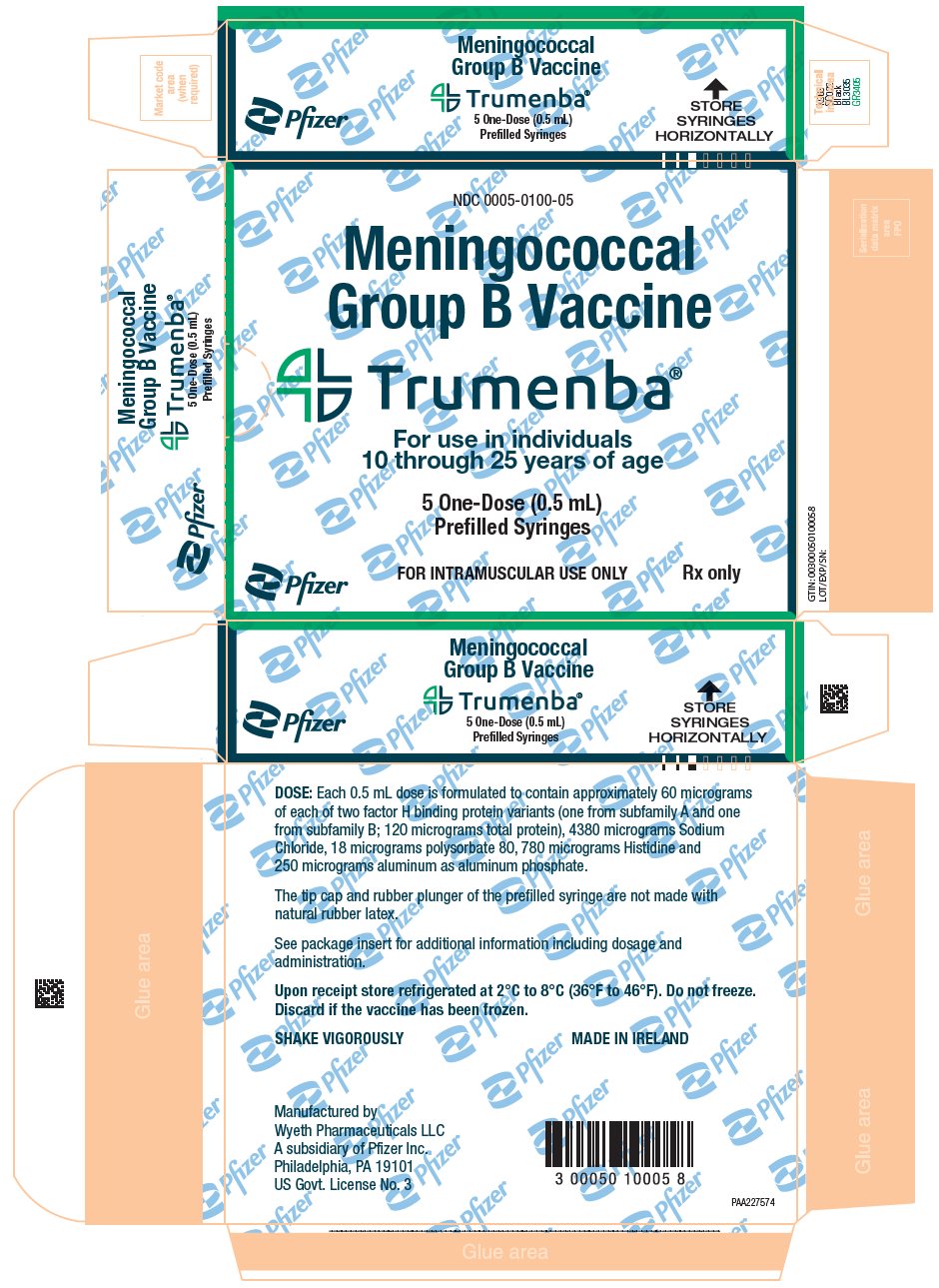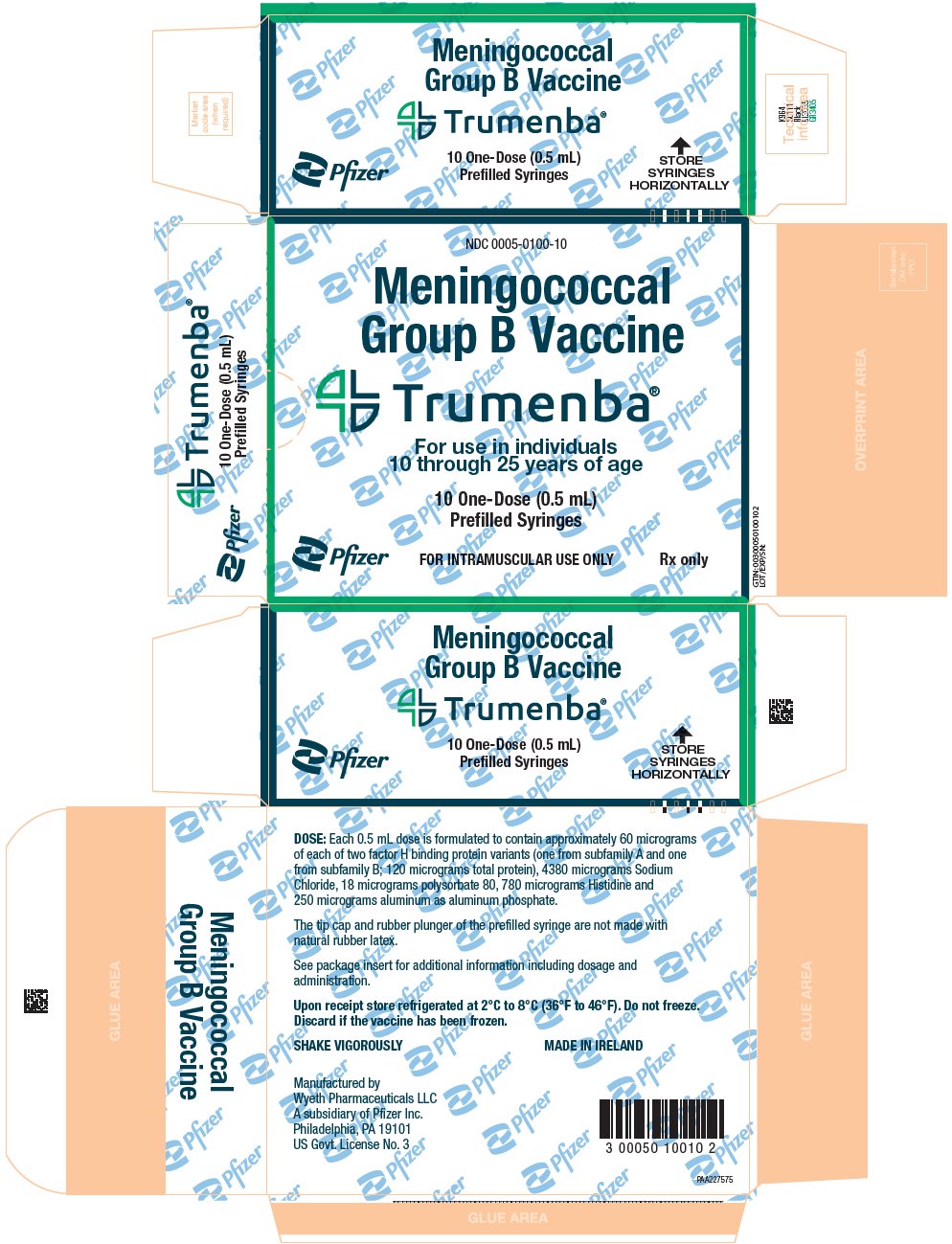 DRUG LABEL: Trumenba
NDC: 0005-0100 | Form: INJECTION, SUSPENSION
Manufacturer: Wyeth Pharmaceutical Division of Wyeth Holdings LLC
Category: other | Type: VACCINE LABEL
Date: 20260119

ACTIVE INGREDIENTS: NEISSERIA MENINGITIDIS GROUP B RECOMBINANT LP2086 A05 PROTEIN VARIANT ANTIGEN 60 ug/0.5 mL; NEISSERIA MENINGITIDIS GROUP B RECOMBINANT LP2086 B01 PROTEIN VARIANT ANTIGEN 60 ug/0.5 mL
INACTIVE INGREDIENTS: POLYSORBATE 80 0.018 mg/0.5 mL; ALUMINUM PHOSPHATE 0.25 mg/0.5 mL; HISTIDINE; SODIUM CHLORIDE; WATER

HIGHLIGHTS OF PRESCRIBING INFORMATION

These highlights do not include all the information needed to use TRUMENBA safely and effectively. See full prescribing information for TRUMENBA.
TRUMENBA® (Meningococcal Group B Vaccine)
Suspension for intramuscular injection
Initial U.S. Approval: 2014

1 INDICATIONS AND USAGE

Trumenba is indicated for active immunization to prevent invasive disease caused by Neisseria meningitidis serogroup B. Trumenba is approved for use in individuals 10 through 25 years of age. (1)

2 DOSAGE AND ADMINISTRATION

- For intramuscular use only. (2)
- Two-dose schedule: Administer a dose (0.5 mL) at 0 and 6 months. If the second dose is administered earlier than 6 months after the first dose, a third dose should be administered at least 4 months after the second dose. (2.1)
- Three-dose schedule: Administer a dose (0.5 mL) at 0, 1–2, and 6 months. (2.1)

3 DOSAGE FORMS AND STRENGTHS

Suspension for intramuscular injection in 0.5 mL single-dose prefilled syringe. (3)

4 CONTRAINDICATIONS

Severe allergic reaction (e.g., anaphylaxis) to any component of Trumenba. (4)

5 WARNINGS AND PRECAUTIONS

Syncope (fainting) can occur in association with administration of injectable vaccines, including Trumenba. Procedures should be in place to avoid injury from fainting. (5.4)

6 ADVERSE REACTIONS

The most common solicited adverse reactions in adolescents and young adults were pain at the injection site (≥85%), fatigue (≥60%), headache (≥55%), and muscle pain (≥35%). (6)
To report SUSPECTED ADVERSE REACTIONS, contact Pfizer Inc. at 1-800-438-1985 or VAERS at 1-800-822-7967 or http://vaers.hhs.gov.

8 USE IN SPECIFIC POPULATIONS

Pediatric Use: Safety and effectiveness have not been established in children <10 years of age. In a clinical study, 90% of infants <12 months of age who were vaccinated with a reduced dosage formulation had fever. (8.4)

FULL PRESCRIBING INFORMATION

1 INDICATIONS AND USAGE

Trumenba is indicated for active immunization to prevent invasive disease caused by Neisseria meningitidis serogroup B. Trumenba is approved for use in individuals 10 through 25 years of age.

2 DOSAGE AND ADMINISTRATION

For intramuscular use only.

2.1 Dose and Schedule

Two-dose schedule: Administer a dose (0.5 mL) at 0 and 6 months. If the second dose is administered earlier than 6 months after the first dose, a third dose should be administered at least 4 months after the second dose.

Three-dose schedule: Administer a dose (0.5 mL) at 0, 1–2, and 6 months.

The choice of dosing schedule may depend on the risk of exposure and the patient's susceptibility to meningococcal serogroup B disease.

2.2 Administration

Shake syringe vigorously to ensure that a homogenous white suspension of Trumenba is obtained. Do not use the vaccine if it cannot be re-suspended. Parenteral drug products should be inspected visually for particulate matter and discoloration prior to administration, whenever solution and container permit. Do not use if particulate matter or discoloration is found.

Inject each 0.5 mL dose intramuscularly, using a sterile needle attached to the supplied prefilled syringe. The preferred site for injection is the deltoid muscle of the upper arm. Do not mix Trumenba with any other vaccine in the same syringe.

2.3 Use of Trumenba with other Meningococcal Group B Vaccines

Data are not available on the safety and effectiveness of using Trumenba and other meningococcal group B vaccines interchangeably to complete the vaccination series.

3 DOSAGE FORMS AND STRENGTHS

Trumenba is a suspension for intramuscular injection in 0.5 mL single-dose prefilled syringe.

4 CONTRAINDICATIONS

Severe allergic reaction (e.g. anaphylaxis) to any component of Trumenba [see Description (11)].

5 WARNINGS AND PRECAUTIONS

5.1 Management of Allergic Reactions

Epinephrine and other appropriate agents used to manage immediate allergic reactions must be immediately available should an acute anaphylactic reaction occur following administration of Trumenba.

5.2 Altered Immunocompetence

Reduced Immune Response

Some individuals with altered immunocompetence may have reduced immune responses to Trumenba.

Complement Deficiency

Persons with certain complement deficiencies and persons receiving treatment that inhibits terminal complement activation (for example, eculizumab) are at increased risk for invasive disease caused by N. meningitidis serogroup B even if they develop antibodies following vaccination with Trumenba [see Clinical Pharmacology (12)].

5.3 Limitation of Vaccine Effectiveness

Vaccination with Trumenba may not protect all vaccine recipients against N. meningitidis serogroup B infections.

5.4 Syncope

Syncope (fainting) can occur in association with administration of injectable vaccines, including Trumenba. Procedures should be in place to avoid injury from fainting.

6 ADVERSE REACTIONS

In clinical studies, the most common solicited adverse reactions in adolescents and young adults were pain at the injection site (≥85%), fatigue (≥60%), headache (≥55%), and muscle pain (≥35%).

6.1 Clinical Trials Experience

Because clinical trials are conducted under widely varying conditions, adverse reaction rates observed in the clinical trials of a vaccine cannot be directly compared to rates in the clinical trials of another vaccine and may not reflect the rates observed in clinical practice.

The safety of Trumenba was evaluated in 16,284 subjects 10 through 25 years of age in 12 clinical studies (9 randomized controlled and 3 supportive non-controlled studies) conducted in the U.S., Europe, Canada, Chile, and Australia. A total of 11,991 subjects 10 through 18 years of age, and 4,293 subjects 19 through 25 years of age received at least one dose of Trumenba. A total of 5,501 subjects 10 through 25 years of age in the control groups received saline placebo and/or one of the following vaccine(s): Human Papillomavirus Quadrivalent (Types 6, 11, 16, and 18) Vaccine, Recombinant (HPV4) (Merck & Co., Inc.); Tetanus Toxoid, Reduced Diphtheria Toxoid and Acellular Pertussis Vaccine Adsorbed (Tdap) (Sanofi Pasteur Ltd.); Meningococcal (Serogroups A, C, Y and W-135) Polysaccharide Diphtheria Toxoid Conjugate Vaccine (MenACWY) (Sanofi Pasteur Inc.); a non-U.S. licensed reduced diphtheria toxoid, tetanus toxoid, acellular pertussis and inactivated polio virus vaccine (dTaP-IPV) (Sanofi Pasteur, Inc.); Hepatitis A Vaccine (HAV) (GlaxoSmithKline Biologicals).

The safety evaluation in the clinical studies included an assessment of: (1) solicited local and systemic reactions, and use of antipyretic medication after each vaccination in an electronic diary maintained by the subject or the subject's parent/legal guardian and (2) spontaneous reports of adverse events (AEs), including serious adverse events (SAEs), throughout the study (day of vaccination through 1 month or 6 months after the last vaccination, depending on the study and safety parameter).

In controlled studies, demographic characteristics were generally similar with regard to gender, race, and ethnicity among subjects who received Trumenba and those who received control. Among participants in clinical trials B1971009 (Study 1009), B1971016 (Study 1016), and B1971057 (Study 1057), 41.3% to 51.5% were male, 76.1% to 87.3% were White, 8.1% to 20.8% were Black or African-American, <2% were Asian, and 5.8% to 17.1% were Hispanic/Latino.

Solicited Local and Systemic Adverse Reactions

Study 1057 was a randomized, observer-blinded, multicenter trial in the U.S. and Europe. In this study, 1057 subjects 10 through 25 years of age received at least 1 dose of Trumenba on a 0- and 6-month schedule. Trumenba was co-administered with Meningococcal (Groups A, C, Y, W-135) Oligosaccharide Diphtheria CRM197 Conjugate Vaccine (MenACWY) (GSK Vaccines, SRL) for the first dose.

Study 1009 was a randomized, active-controlled, observer-blinded, multicenter trial in the U.S., Canada, and Europe in which 2,693 subjects 10 through 18 years of age received at least 1 dose of Trumenba on a 0-, 2-, and 6- month schedule. A control group (n=897) received HAV at 0 and 6 months, and saline at 2 months.

Study 1016 was a randomized, placebo-controlled, observer-blinded, multicenter trial in the U.S., Canada, and Europe in which 2,471 subjects 18 through 25 years of age received at least 1 dose of Trumenba and 822 subjects received saline on a 0-, 2,- and 6- month schedule.

Local adverse reactions at the injection site were assessed in the three studies.

Tables 1, 2, and 3 present the percentage and severity of reported local adverse reactions within 7 days following each dose of Trumenba for Study 1057 and following each dose of Trumenba or control (HAV/saline or saline) for Study 1009 and Study 1016, respectively.

In Studies 1009 and 1016, local adverse reactions were reported more frequently following Trumenba compared to control (see Tables 2 and 3, respectively).

Table 1: Percentages of Subjects 10 through 25 Years of Age (Study 1057 [Study 1057: National Clinical Trial (NCT) number NCT03135834.]) Reporting Local Adverse Reactions Within 7 Days After Each Vaccination
Local Reaction | Dose 1 | Dose 2
Local Reaction | Trumenba+MenACWY-CRM [Trumenba and MenACWY-CRM were administered at 0 month followed by Trumenba alone at 6 months. Local reactions were recorded at the Trumenba injection site only.] | Trumenba
Local Reaction | N=1044 | N=903
Pain [Mild (does not interfere with activity); moderate (interferes with activity); severe (prevents daily activity).]
Any ["Any" is defined as the cumulative frequency of subjects who reported a reaction as "mild", "moderate", or "severe" within 7 days of vaccination.] | 85.0 | 82.2
Mild | 41.2 | 38.9
Moderate | 39.1 | 37.9
Severe | 4.7 | 5.4
Redness [Mild (2.5–5.0 cm); moderate (>5.0–10.0 cm); severe (>10.0 cm).]
Any (≥ 2.5 cm) | 16.9 | 14.7
Mild | 6.8 | 5.2
Moderate | 8.0 | 8.4
Severe | 2.0 | 1.1
Swelling
Any (≥ 2.5 cm) | 17.0 | 14.3
Mild | 9.8 | 6.4
Moderate | 6.9 | 7.5
Severe | 0.3 | 0.3

Table 2: Percentages of Subjects 10 through 18 Years of Age (Study 1009 [Study 1009: NCT01830855.]) Reporting Local Adverse Reactions Within 7 Days After Each Vaccination
 | Dose 1 |  | Dose 2 |  | Dose 3
 | Trumenba [Trumenba was administered at 0, 2, and 6 months. HAV was administered at 0 and 6 months and saline was administered at 2 months.] | HAV/Saline | Trumenba | HAV/Saline | Trumenba | HAV/Saline
Local Reaction | N=2681 | N=890 | N=2545 | N=843 | N=2421 | N=821
Pain [Mild (does not interfere with activity); moderate (interferes with activity); severe (prevents daily activity).]
Any ["Any" is defined as the cumulative frequency of subjects who reported a reaction as "mild", "moderate", or "severe" within 7 days of vaccination.] | 86.7 | 47.0 | 77.7 | 15.2 | 76.0 | 34.0
Mild | 41.1 | 36.5 | 39.4 | 12.3 | 34.1 | 23.8
Moderate | 40.7 | 9.9 | 33.2 | 2.7 | 36.5 | 9.9
Severe | 5.0 | 0.6 | 5.1 | 0.1 | 5.4 | 0.4
Redness [Mild (2.5–5.0 cm); moderate (>5.0–10.0 cm); severe (>10.0 cm).]
Any (≥ 2.5 cm) | 16.2 | 1.3 | 12.5 | 0.6 | 13.9 | 1.1
Mild | 5.6 | 1.2 | 5.2 | 0.6 | 4.9 | 1.0
Moderate | 8.8 | 0.1 | 6.1 | 0.0 | 6.8 | 0.1
Severe | 1.9 | 0.0 | 1.1 | 0.0 | 2.2 | 0.0
Swelling
Any (≥ 2.5 cm) | 18.0 | 2.2 | 13.9 | 0.6 | 15.4 | 0.9
Mild | 8.5 | 1.8 | 6.3 | 0.5 | 7.9 | 0.7
Moderate | 8.8 | 0.4 | 7.3 | 0.1 | 6.8 | 0.1
Severe | 0.7 | 0.0 | 0.2 | 0.0 | 0.7 | 0.0

Table 3: Percentages of Subjects 18 through 25 Years of Age (Study 1016 [Study 1016: NCT01352845.]) Reporting Local Adverse Reactions Within 7 Days After Each Vaccination
 | Dose 1 |  | Dose 2 |  | Dose 3
 | Trumenba [Trumenba was administered at 0, 2, and 6 months. Saline was administered at 0, 2, and 6 months.] | Saline | Trumenba | Saline | Trumenba | Saline
Local Reaction | N=2425 | N=798 | N=2076 | N=706 | N=1823 | N=624
Pain [Mild (does not interfere with activity); moderate (interferes with activity); severe (prevents daily activity).]
Any ["Any" is defined as the cumulative frequency of subjects who reported a reaction as "mild", "moderate", or "severe" within 7 days of vaccination.] | 84.2 | 11.8 | 79.3 | 7.8 | 80.4 | 6.7
Mild | 42.3 | 10.7 | 42.2 | 6.8 | 36.1 | 6.4
Moderate | 37.1 | 1.1 | 32.7 | 1.0 | 38.9 | 0.3
Severe | 4.8 | 0.0 | 4.4 | 0.0 | 5.3 | 0.0
Redness [Mild (2.5–5.0 cm); moderate (>5.0–10.0 cm); severe (>10.0 cm).]
Any (≥ 2.5 cm) | 13.8 | 0.6 | 11.8 | 0.3 | 17.1 | 0.2
Mild | 5.8 | 0.5 | 4.6 | 0.1 | 6.2 | 0.2
Moderate | 7.1 | 0.0 | 6.3 | 0.0 | 8.6 | 0.0
Severe | 0.9 | 0.1 | 0.9 | 0.1 | 2.3 | 0.0
Swelling
Any (≥ 2.5 cm) | 15.5 | 0.6 | 14.0 | 0.4 | 16.6 | 0.3
Mild | 8.5 | 0.3 | 7.7 | 0.3 | 8.8 | 0.0
Moderate | 6.8 | 0.3 | 6.0 | 0.1 | 7.2 | 0.3
Severe | 0.2 | 0.1 | 0.3 | 0.0 | 0.5 | 0.0

In Study 1057, among Trumenba recipients, mean duration of pain was 2.7 days (range 1–17 days) after the first vaccination and 2.7 days (range 1–12 days) after the second vaccination; redness was 2.2 days (range 1–9 days) and 2.4 days (1–11 days), respectively; and swelling was 2.2 days (range 1–17 days) and 2.5 days (range 1–27 days), respectively.

In Study 1009, mean duration of pain was 2.4 to 2.6 days (range 1–17 days), redness was 2.0 to 2.2 days (range 1–12 days) and swelling was 2.0 to 2.1 days (range 1–21 days) for the three-dose series in the Trumenba groups. In Study 1016, mean duration of pain was 2.6 to 2.8 days (range 1–67 days), redness was 2.2 to 2.5 days (range 1–13 days) and swelling was 2.1 to 2.6 days (range 1–70 days) in the Trumenba group.

Tables 4, 5, and 6 present the percentage and severity of reported solicited systemic adverse reactions within 7 days of each dose of Trumenba for Study 1057 and within 7 days of each dose of Trumenba or control (HAV/saline or saline) for Study 1009 and Study 1016, respectively.

Table 4: Percentages of Subjects 10 through 25 Years of Age (Study 1057 [Study 1057: NCT03135834.]) Reporting Systemic Adverse Reactions and Use of Antipyretic Medications Within 7 Days After Each Vaccination
Systemic Reaction | Dose 1 | Dose 2
Systemic Reaction | Trumenba+MenACWY-CRM [Trumenba and MenACWY-CRM were administered at 0 month followed by Trumenba alone at 6 months.] | Trumenba
Systemic Reaction | N=1044 | N=903
Fever (≥38°C)
≥38.0°C | 6.7 | 3.2
38.0°C to <38.5°C | 4.0 | 1.9
38.5°C to <39.0°C | 2.1 | 0.7
39.0°C to ≤40.0°C | 0.6 | 0.7
>40.0°C | 0.0 | 0.0
Vomiting [Mild (1–2 times in 24 hours); moderate (>2 times in 24 hours); severe (requires intravenous hydration).]
Any ["Any" is defined as the cumulative frequency of subjects who reported a reaction as "mild", "moderate", or "severe" within 7 days of vaccination.] | 3.7 | 2.8
Mild | 2.9 | 2.0
Moderate | 0.9 | 0.8
Severe | 0.0 | 0.0
Diarrhea [Mild (2–3 loose stools in 24 hours); moderate (4–5 loose stools in 24 hours); severe (6 or more loose stools in 24 hours).]
Any | 14.1 | 10.6
Mild | 10.7 | 7.6
Moderate | 3.3 | 2.5
Severe | 0.1 | 0.4
Headache [Mild (does not interfere with activity); moderate (some interference with activity); severe (prevents daily routine activity).]
Any | 46.5 | 41.6
Mild | 25.1 | 23.1
Moderate | 19.0 | 16.5
Severe | 2.4 | 2.0
Fatigue
Any | 51.9 | 45.2
Mild | 25.4 | 23.0
Moderate | 23.7 | 19.2
Severe | 2.9 | 3.0
Chills
Any | 18.5 | 18.5
Mild | 11.5 | 11.6
Moderate | 5.7 | 6.2
Severe | 1.2 | 0.7
Muscle pain (other than muscle pain at the injection site)
Any | 28.4 | 21.4
Mild | 15.8 | 11.5
Moderate | 11.6 | 7.8
Severe | 1.1 | 2.1
Joint pain
Any | 19.6 | 18.7
Mild | 10.2 | 11.2
Moderate | 8.6 | 6.5
Severe | 0.8 | 1.0
Use of antipyretic medication | 18.6 | 14.4

Table 5: Percentages of Subjects 10 through 18 Years of Age (Study 1009 [Study 1009: NCT01830855.]) Reporting Systemic Adverse Reactions and Use of Antipyretic Medications Within 7 Days After Each Vaccination
 | Dose 1 |  | Dose 2 |  | Dose 3
 | Trumenba [Trumenba was administered at 0, 2, and 6 months. HAV was administered at 0 and 6 months and saline was administered at 2 months.] | HAV/Saline | Trumenba | HAV/Saline | Trumenba | HAV/Saline
Systemic Reaction | N=2681 | N=890 | N=2545 | N=843 | N=2421 | N=821
Fever (≥38°C) [Study 1009: Fever (≥38°C): N=2679, 2540, and 2414 for Trumenba at Dose 1, Dose 2, and Dose 3, respectively; N=890, 840, and 819 for HAV/saline at Dose 1, Dose 2, and Dose 3, respectively.]
≥38.0°C | 6.4 | 1.9 | 2.0 | 1.5 | 2.7 | 2.3
38.0°C to <38.5°C | 4.0 | 1.3 | 1.2 | 0.7 | 1.8 | 1.3
38.5°C to <39.0°C | 1.9 | 0.3 | 0.7 | 0.7 | 0.6 | 0.4
39.0°C to ≤40.0°C | 0.5 | 0.2 | 0.1 | 0.1 | 0.3 | 0.5
>40.0°C | 0.0 | 0.0 | 0.0 | 0.0 | 0.0 | 0.1
Vomiting [Mild (1–2 times in 24 hours); moderate (>2 times in 24 hours); severe (requires intravenous hydration).]
Any ["Any" is defined as the cumulative frequency of subjects who reported a reaction as "mild", "moderate", or "severe" within 7 days of vaccination.] | 3.7 | 1.9 | 2.2 | 1.4 | 1.7 | 2.2
Mild | 2.8 | 1.7 | 1.7 | 1.1 | 1.4 | 1.7
Moderate | 0.9 | 0.2 | 0.4 | 0.4 | 0.3 | 0.5
Severe | 0.0 | 0.0 | 0.0 | 0.0 | 0.0 | 0.0
Diarrhea [Mild (2–3 loose stools in 24 hours); moderate (4–5 loose stools in 24 hours); severe (6 or more loose stools in 24 hours).]
Any | 10.6 | 12.1 | 7.6 | 9.1 | 7.7 | 7.6
Mild | 9.1 | 10.9 | 6.2 | 7.6 | 6.4 | 6.2
Moderate | 1.3 | 1.1 | 1.3 | 1.2 | 1.0 | 1.1
Severe | 0.3 | 0.1 | 0.1 | 0.4 | 0.3 | 0.2
Headache [Mild (does not interfere with activity); moderate (interferes with activity); severe (prevents daily activity).]
Any | 51.8 | 37.2 | 37.8 | 28.1 | 35.4 | 24.8
Mild | 28.7 | 24.0 | 20.2 | 15.7 | 18.9 | 13.5
Moderate | 21.0 | 12.5 | 16.0 | 10.9 | 15.2 | 10.4
Severe | 2.2 | 0.7 | 1.7 | 1.5 | 1.3 | 1.0
Fatigue
Any | 54.0 | 40.3 | 38.3 | 26.3 | 35.9 | 24.4
Mild | 27.8 | 23.5 | 20.6 | 13.2 | 18.4 | 13.5
Moderate | 23.2 | 15.2 | 15.8 | 11.7 | 15.2 | 10.0
Severe | 3.0 | 1.7 | 1.9 | 1.4 | 2.3 | 0.9
Chills
Any | 25.3 | 17.2 | 16.0 | 10.3 | 13.1 | 8.3
Mild | 16.2 | 13.3 | 10.6 | 8.1 | 8.7 | 6.5
Moderate | 8.0 | 3.5 | 4.8 | 1.8 | 3.8 | 1.7
Severe | 1.2 | 0.4 | 0.6 | 0.5 | 0.5 | 0.1
Muscle pain (other than muscle pain at the injection site)
Any | 24.4 | 19.2 | 17.8 | 10.3 | 17.6 | 11.1
Mild | 13.2 | 13.5 | 8.7 | 5.2 | 9.5 | 6.6
Moderate | 10.1 | 5.4 | 7.9 | 4.5 | 7.2 | 4.3
Severe | 1.2 | 0.3 | 1.2 | 0.6 | 0.8 | 0.2
Joint pain
Any | 21.9 | 13.6 | 16.7 | 9.1 | 16.0 | 8.9
Mild | 11.8 | 8.3 | 8.4 | 5.0 | 8.9 | 5.5
Moderate | 8.7 | 4.6 | 7.5 | 3.4 | 5.9 | 3.0
Severe | 1.4 | 0.7 | 0.8 | 0.7 | 1.2 | 0.4
Use of antipyretic medication | 20.7 | 10.4 | 13.6 | 8.9 | 12.7 | 6.8

Table 6: Percentages of Subjects 18 through 25 Years of Age (Study 1016 [Study 1016: NCT01352845.]) Reporting Systemic Adverse Reactions and Use of Antipyretic Medications Within 7 Days After Each Vaccination
 | Dose 1 |  | Dose 2 |  | Dose 3
 | Trumenba [Trumenba was administered at 0, 2, and 6 months. Saline was administered at 0, 2, and 6 months.] | Saline | Trumenba | Saline | Trumenba | Saline
Systemic Reaction | N=2425 | N=798 | N=2076 | N=706 | N=1823 | N=624
Fever (≥38°C) [Study 1016: Fever (≥38°C): N=2415, 2067, and 1814 for Trumenba at Dose 1, Dose 2, and Dose 3, respectively; N=796, 705, and 621 for saline at Dose 1, Dose 2, and Dose 3, respectively.]
≥38.0°C | 2.4 | 0.6 | 1.2 | 1.0 | 2.0 | 0.6
38.0°C to <38.5°C | 1.6 | 0.4 | 0.7 | 0.6 | 1.4 | 0.5
38.5°C to <39.0°C | 0.7 | 0.0 | 0.4 | 0.3 | 0.4 | 0.2
39.0°C to ≤40.0°C | 0.0 | 0.3 | 0.1 | 0.1 | 0.1 | 0.0
>40.0°C | 0.0 | 0.0 | 0.0 | 0.0 | 0.1 | 0.0
Vomiting [Mild (1–2 times in 24 hours); moderate (>2 times in 24 hours); severe (requires intravenous hydration).]
Any ["Any" is defined as the cumulative frequency of subjects who reported a reaction as "mild", "moderate", or "severe" within 7 days of vaccination.] | 2.6 | 2.1 | 2.1 | 1.6 | 2.0 | 1.4
Mild | 2.2 | 2.1 | 1.6 | 1.3 | 1.8 | 1.1
Moderate | 0.4 | 0.0 | 0.5 | 0.3 | 0.2 | 0.3
Severe | 0.0 | 0.0 | 0.0 | 0.0 | 0.0 | 0.0
Diarrhea [Mild (2–3 loose stools in 24 hours); moderate (4–5 loose stools in 24 hours); severe (6 or more loose stools in 24 hours).]
Any | 12.7 | 11.8 | 8.6 | 8.1 | 7.5 | 6.9
Mild | 10.2 | 9.8 | 6.4 | 4.7 | 6.1 | 5.3
Moderate | 2.4 | 1.9 | 1.7 | 2.8 | 1.2 | 1.3
Severe | 0.2 | 0.1 | 0.5 | 0.6 | 0.2 | 0.3
Headache [Mild (does not interfere with activity); moderate (interferes with activity); severe (prevents daily activity).]
Any | 43.9 | 36.2 | 33.1 | 24.9 | 32.5 | 21.6
Mild | 24.3 | 22.1 | 18.4 | 13.6 | 17.6 | 12.5
Moderate | 17.9 | 13.5 | 13.3 | 10.1 | 13.3 | 8.3
Severe | 1.6 | 0.6 | 1.4 | 1.3 | 1.6 | 0.8
Fatigue
Any | 50.9 | 39.8 | 39.2 | 27.3 | 39.3 | 24.5
Mild | 25.4 | 23.2 | 20.6 | 13.9 | 18.9 | 13.1
Moderate | 22.1 | 15.8 | 16.4 | 11.5 | 18.8 | 9.6
Severe | 3.4 | 0.9 | 2.2 | 2.0 | 1.6 | 1.8
Chills
Any | 18.1 | 9.8 | 12.4 | 8.5 | 12.6 | 6.4
Mild | 12.0 | 8.1 | 8.1 | 6.9 | 7.7 | 4.3
Moderate | 4.9 | 1.6 | 3.5 | 1.6 | 4.2 | 2.1
Severe | 1.1 | 0.0 | 0.8 | 0.0 | 0.8 | 0.0
Muscle pain (other than muscle pain at the injection site)
Any | 25.9 | 14.5 | 15.6 | 8.5 | 16.9 | 7.5
Mild | 13.0 | 9.6 | 7.6 | 5.8 | 8.9 | 4.5
Moderate | 11.3 | 4.4 | 7.1 | 2.3 | 6.8 | 2.9
Severe | 1.6 | 0.5 | 0.8 | 0.4 | 1.2 | 0.2
Joint pain
Any | 19.6 | 10.9 | 15.1 | 6.5 | 12.6 | 5.3
Mild | 10.3 | 6.9 | 8.1 | 3.7 | 6.6 | 2.9
Moderate | 7.9 | 3.5 | 6.2 | 2.5 | 5.4 | 2.4
Severe | 1.4 | 0.5 | 0.9 | 0.3 | 0.6 | 0.0
Use of antipyretic medication | 13.4 | 8.9 | 12.3 | 7.6 | 12.8 | 6.6

In three early phase studies in which it was solicited, nausea was reported in up to 24% of adolescents.

The frequencies of adverse reactions were highest after the first dose regardless of the schedule. After subsequent doses, the frequencies of adverse reactions were similar regardless of dose number and schedule.

Serious Adverse Events

Among the 8 controlled studies investigating the three-dose (0, 1–2, and 6 months) schedule (Trumenba N=13,275, control N=5,501), SAEs were reported by 213 (1.6%) subjects and by 106 (1.9%) subjects who received at least one dose of Trumenba or control, respectively.

Non-serious Adverse Events

Among the 8 controlled studies investigating the three-dose (0, 1–2, and 6 months) schedule (Trumenba N=13,275, control N=5,501), AEs that occurred within 30 days of vaccination were reported in 4,056 (30.6%) subjects who received at least one dose of Trumenba and 1,539 (28.0%) subjects in the control group who received at least one dose. AEs that occurred at a frequency of at least 2% and were more frequently observed in subjects who received Trumenba than subjects in the control group were injection site pain, fever, and headache.

6.2 Postmarketing Experience

The following adverse reactions have been identified during post-approval use of Trumenba. Because these reactions are reported voluntarily from a population of uncertain size, it is not always possible to reliably estimate their frequency or establish a causal relationship to product exposure.

Immune System Disorders: Hypersensitivity reactions, including anaphylactic reactions.

Nervous system disorder: Syncope (fainting).

7 DRUG INTERACTIONS

In clinical trials, Trumenba was administered concomitantly with HPV4 in adolescents 11 through 17 years of age and with MenACWY and Tdap in adolescents 10 through 12 years of age [see Clinical Studies (14) and Adverse Reactions (6)].

8 USE IN SPECIFIC POPULATIONS

8.1 Pregnancy

Risk Summary

All pregnancies have a risk of birth defect, loss, or other adverse outcomes. In the U.S. general population, the estimated background risk of major birth defects and miscarriage in clinically recognized pregnancies is 2% to 4% and 15% to 20%, respectively. There are no adequate and well-controlled studies of Trumenba in pregnant women. Available human data on Trumenba administered to pregnant women are insufficient to inform vaccine-associated risks in pregnancy.

Two developmental toxicity studies were performed in female rabbits administered Trumenba prior to mating and during gestation. The dose was 0.5 mL at each occasion (a single human dose is 0.5 mL). These studies revealed no evidence of harm to the fetus or offspring (until weaning) due to Trumenba [see Animal Data].

Animal Data

Two developmental toxicity studies were performed in female rabbits. Animals were administered Trumenba by intramuscular injection 17 days and 4 days prior to mating and on gestation Days 10 and 24. The dose was 0.5 mL at each occasion (a single human dose is 0.5 mL). No adverse effects on pre-weaning development up to post-natal day 21 were observed. There were no fetal malformations or variations observed due to the vaccine.

8.2 Lactation

Risk Summary

Available data are not sufficient to assess the effects of Trumenba on the breastfed infant or on milk production/excretion. The developmental and health benefits of breastfeeding should be considered along with the mother's clinical need for Trumenba and any potential adverse effects on the breastfed child from Trumenba or from the underlying maternal condition. For preventive vaccines, the underlying maternal condition is susceptibility to disease prevented by the vaccine.

8.4 Pediatric Use

Safety and effectiveness have not been established in children <10 years of age. In a clinical study, 90% of infants <12 months of age who were vaccinated with a reduced dosage formulation had fever. Clinical data strongly suggest that a two-dose regimen of Trumenba would be ineffective in children 1 to <10 years of age.

8.5 Geriatric Use

Safety and effectiveness of Trumenba in adults >65 years of age have not been established.

11 DESCRIPTION

Trumenba is a sterile suspension composed of two recombinant lipidated factor H binding protein (fHbp) variants from N. meningitidis serogroup B, one from fHbp subfamily A and one from subfamily B (A05 and B01, respectively).^1 The proteins are individually produced in E. coli. Production strains are grown in defined fermentation growth media to a specific density. The recombinant proteins are extracted from the production strains and purified through a series of column chromatography steps. Polysorbate 80 (PS80) is added to the drug substances and is present in the final drug product.

Each 0.5 mL dose contains 60 micrograms of each fHbp variant (total of 120 micrograms of protein), 0.018 mg of PS80 and 0.25 mg of Al^3+ as AlPO4 in 10 mM histidine buffered saline at pH 6.0.

12 CLINICAL PHARMACOLOGY

12.1 Mechanism of Action

Protection against invasive meningococcal disease is conferred mainly by complement-mediated antibody-dependent killing of N. meningitidis. The effectiveness of Trumenba was assessed by measuring serum bactericidal activity using human complement (hSBA).

fHbp is one of many proteins found on the surface of meningococci and contributes to the ability of the bacterium to avoid host defenses. fHbps can be categorized into two immunologically distinct subfamilies, A and B.^1 The susceptibility of serogroup B meningococci to complement-mediated antibody-dependent killing following vaccination with Trumenba is dependent on both the antigenic similarity of the bacterial and vaccine fHbps, as well as the amount of fHbp expressed on the surface of the invading meningococci.

13 NONCLINICAL TOXICOLOGY

Trumenba has not been evaluated for carcinogenic or mutagenic potential or impairment of fertility in males. Vaccination of female rabbits with Trumenba had no effect on fertility [see Pregnancy (8.1)].

14 CLINICAL STUDIES

The immunogenicity of Trumenba described in this section is based on results from four clinical studies:

- Following the two-dose schedule (0 and 6 months) in subjects 10 through 25 years of age in the U.S. and Europe (Study 1057);
- Following the three-dose schedule (0, 2, and 6 months) in subjects 10 through 25 years of age in the U.S., Canada, and Europe (Studies 1009 and 1016); and
- Following the two-dose (0 and 6 months) and three-dose schedules (0, 1–2, and 6 months) in subjects 11 through 18 years of age in Europe (Study 1012).

Serum bactericidal antibodies were measured with hSBA assays that used each of four meningococcal serogroup B strains. These four primary test strains express fHbp variants representing the two subfamilies (A and B) of meningococcal serogroup B strains causing invasive disease in the U.S. and Europe. The studies assessed the proportions of subjects with a 4-fold or greater increase in hSBA titer for each of the four primary strains. The studies also assessed the composite response to the four primary strains combined (proportion of subjects who achieved a hSBA titer greater than or equal to 1:8 [three strains] and 1:16 [one strain]). To assess the effectiveness of the two- and three-dose schedules of Trumenba against diverse meningococcal serogroup B strains, the proportion of subjects achieving a defined hSBA titer (≥LLOQ) following completion of the two- or three-dose series was evaluated against a panel of 10 additional strains, each expressing a different fHbp variant.

14.1 Immunogenicity

The hSBA responses to each of the primary strains observed after the second dose of Trumenba in Study 1057 are presented in Table 7.

Table 7: Percentages of Subjects 10 through 25 Years of Age With ≥4-fold Rise in hSBA Titer and Composite Response Following Administration of Trumenba on a 0-and 6-Month Schedule for Four Primary Strains (Study 1057) [Evaluable immunogenicity population.] , [Study 1057: NCT03135834.]
fHbp Variant [For the second dose, serum was obtained approximately 1 month after vaccination.] |  | N [For ≥4-fold increase, N=number of subjects with valid and determinate hSBA titers for the given strain at both the specified time point and baseline. For composite hSBA response, N=number of subjects with valid and determinate hSBA results on all 4 strains at the given time point. U.S. subjects constituted approximately 80% of the total subjects evaluated for immunogenicity.] | % (95% CI) [Exact 2-sided confidence interval (Clopper-Pearson method) based upon the observed proportion of subjects.]
≥4-Fold Increase
PMB80 (A22) | Dose 2 | 827 | 73.8 (70.6, 76.7)
PMB2001 (A56) | Dose 2 | 823 | 95.0 (93.3, 96.4)
PMB2948 (B24) | Dose 2 | 835 | 67.4 (64.1, 70.6)
PMB2707 (B44) | Dose 2 | 850 | 86.4 (83.9, 88.6)
Composite hSBA Response [Composite response = hSBA ≥ LLOQ for all 4 primary meningococcal B strains.]
 | Before Dose 1 | 799 | 1.8 (1.0, 2.9)
 | Dose 2 | 814 | 74.3 (71.2, 77.3)
Abbreviations: CI=confidence interval; fHbp=factor H binding protein; hSBA=serum bactericidal assay using human complement; LLOQ=lower limit of quantitation; LOD=limit of detection.
Note: LLOQ = 1:16 for A22; 1:8 for A56, B24, and B44.
Note: The 4-fold increase is defined as follows: (1) For subjects with a baseline hSBA titer <1:4, a response is defined as an hSBA titer ≥1:16. (2) For subjects with a baseline hSBA titer ≥ LOD and < LLOQ, a response is defined as an hSBA titer ≥4 times the LLOQ. (3) For subjects with a baseline hSBA titer ≥ LLOQ, a response is defined as an hSBA titer ≥4 times the baseline titer.
Note: Pre-specified criteria for assessment of hSBA responses (4-fold rise in titer to each primary test strain, and titer above LLOQ for all four primary test strains) among subjects in the U.S. and Europe were met in this study for all test strains except strain A22. Pre-specified criteria for the lower bound of the 95% CI for 4-fold rise in titer were set at 75%, 85%, 55%, and 60%, respectively, for A22, A56, B24, and B44, and 65% for the composite hSBA response for all four primary test strains.

The hSBA responses after the second dose of Trumenba in Study 1057 against a panel of 10 additional strains representing the diversity of meningococcal fHbp types prevalent among strains circulating in the US are presented in Table 8.

Table 8. Percentages of Subjects 10 through 25 Years of Age With a hSBA Titer ≥ LLOQ Against 10 Additional Strains Following Administration of Trumenba on a 0- and 6-Month Schedule (Study 1057) [The evaluable immunogenicity population was used for the analysis.] , [Study 1057: NCT03135834.]
fHbp Variant [For the second dose, serum was obtained approximately 1 month after vaccination.] |  | N [N=number of subjects with valid and determinate hSBA titers for the given strain. U.S. subjects constituted approximately 80% of the total subjects evaluated for immunogenicity.] | % (95% CI) [Exact 2-sided confidence interval (Clopper and Pearson) based upon the observed proportion of subjects.]
PMB3175 (A29) | Before Dose 1 | 166 | 4.8 (2.1, 9.3)
PMB3175 (A29) | Dose 2 | 166 | 95.2 (90.7, 97.9)
PMB3010 (A06) | Before Dose 1 | 157 | 5.7 (2.7, 10.6)
PMB3010 (A06) | Dose 2 | 159 | 89.3 (83.4, 93.6)
PMB3040 (A07) | Before Dose 1 | 150 | 32.0 (24.6, 40.1)
PMB3040 (A07) | Dose 2 | 157 | 96.8 (92.7, 99.0)
PMB824 (A12) | Before Dose 1 | 154 | 5.2 (2.3, 10.0)
PMB824 (A12) | Dose 2 | 157 | 83.4 (76.7, 88.9)
PMB1672 (A15) | Before Dose 1 | 166 | 22.9 (16.7, 30.0)
PMB1672 (A15) | Dose 2 | 165 | 89.1 (83.3, 93.4)
PMB1989 (A19) | Before Dose 1 | 167 | 5.4 (2.5, 10.0)
PMB1989 (A19) | Dose 2 | 167 | 90.4 (84.9, 94.4)
PMB1256 (B03) | Before Dose 1 | 172 | 3.5 (1.3, 7.4)
 | Dose 2 | 164 | 74.4 (67.0, 80.9)
PMB866 (B09) | Before Dose 1 | 171 | 9.9 (5.9, 15.4)
PMB866 (B09) | Dose 2 | 166 | 71.1 (63.6, 77.8)
PMB431 (B15) | Before Dose 1 | 172 | 6.4 (3.2, 11.2)
PMB431 (B15) | Dose 2 | 167 | 85.0 (78.7, 90.1)
PMB648 (B16) | Before Dose 1 | 172 | 8.1 (4.5, 13.3)
PMB648 (B16) | Dose 2 | 164 | 77.4 (70.3, 83.6)
Abbreviations: CI=confidence interval; fHbp=factor H binding protein; hSBA=serum bactericidal assay using human complement; LLOQ=lower limit of quantitation.
Note: LLOQ = 1:16 for A06, A12, and A19; 1:8 for A07, A15, A29, B03, B09, B15, and B16.

The hSBA responses to each of the primary strains observed in U.S. subjects after the third dose of Trumenba are presented for Study 1009 and Study 1016 in Table 9.

Table 9: Percentages of U.S. Subjects 10 through 25 Years of Age With ≥4-fold Rise in hSBA Titer and Composite Response Following Administration of Trumenba on a 0-, 2-, and 6-Month Schedule for Four Primary Strains (Studies 1009 and 1016) [Evaluable immunogenicity population.] , [Study 1009: NCT01830855, and Study 1016: NCT01352845.] , [Study 1009: Group 1 (0, 2, and 6 months).] , [Study 1016: Group 1 (0, 2, and 6 months).]
 |  | Study 1009 |  | Study 1016
 |  | (10 through 18 Years of Age) |  | (18 through 25 Years of Age)
 |  | N [For ≥4-fold increase, N=number of subjects with valid and determinate hSBA titers for the given strain at both the specified time point and baseline. For composite hSBA response, N=number of subjects with valid and determinate hSBA results on all 4 strains at the given time point.] | % (95% CI) [Exact 2-sided confidence interval (Clopper-Pearson method) based upon the observed proportion of subjects.] | N | % (95% CI)
fHbp Variant [For the third dose, serum was obtained approximately 1 month after vaccination.]
≥4-Fold Increase
PMB80 (A22) | Dose 3 | 587 | 86.2 (83.1, 88.9) | 644 | 81.1 (77.8, 84.0)
PMB2001 (A56) | Dose 3 | 526 | 92.0 (89.4, 94.2) | 621 | 90.7 (88.1, 92.8)
PMB2948 (B24) | Dose 3 | 585 | 81.9 (78.5, 84.9) | 634 | 83.9 (80.8, 86.7)
PMB2707 (B44) | Dose 3 | 555 | 88.3 (85.3, 90.8) | 643 | 79.3 (76.0, 82.4)
Composite hSBA Response [Composite response = hSBA ≥ LLOQ for all 4 primary meningococcal B strains.]
 | Before Dose 1 | 507 | 0.6 (0.1, 1.7) | 610 | 3.3 (2.0, 5.0)
 | Dose 3 | 537 | 85.7 (82.4, 88.5) | 625 | 82.4 (79.2, 85.3)
Abbreviations: CI=confidence interval; fHbp=factor H binding protein; hSBA=serum bactericidal assay using human complement; LLOQ=lower limit of quantitation; LOD=limit of detection.
Note: LLOQ = 1:16 for A22; 1:8 for A56, B24, and B44.
Note: The 4-fold increase is defined as follows: (1) For subjects with a baseline hSBA titer <1:4, a response is defined as an hSBA titer ≥1:16. (2) For subjects with a baseline hSBA titer ≥ LOD and < LLOQ, a response is defined as an hSBA titer ≥4 times the LLOQ. (3) For subjects with a baseline hSBA titer ≥ LLOQ, a response is defined as an hSBA titer ≥4 times the baseline titer.
Note: Pre-specified criteria for assessment of hSBA responses (4-fold rise in titer to each primary test strain, and titer above LLOQ for all four primary test strains) among U.S. subjects were met in these studies. For Study 1009 pre-specified criteria for the lower bound of the 95% CI for 4-fold rise in titer were set at 75%, 85%, 65%, and 60%, respectively, for A22, A56, B24 and B44, and 75% for the composite hSBA response for all four primary test strains. For Study 1016 pre-specified criteria for the lower bound of the 95% CI for 4-fold rise in titer were set at 55%, 85%, 50%, and 60%, respectively, for A22, A56, B24, and B44, and 60% for the composite hSBA response for all four primary test strains.

The hSBA responses after the third dose of Trumenba against a panel of 10 additional strains representing the diversity of meningococcal fHbp types prevalent among strains circulating in the U.S. are presented for Study 1009, and Study 1016 in Table10.

Table 10. Percentages of U.S. Subjects 10 through 25 Years of Age With a hSBA Titer ≥ LLOQ Against 10 Additional Strains Following Administration of Trumenba on a 0-, 2-, and 6-Month Schedule (Study 1009 and Study 1016) [The evaluable immunogenicity population was used for the analysis.] , [Study 1009: NCT01830855 and Study 1016 NCT01352845.]
fHbp Variant [For the third dose, serum was obtained approximately 1 month after vaccination.] |  | Study 1009 |  | Study 1016
fHbp Variant [For the third dose, serum was obtained approximately 1 month after vaccination.] |  | (10 through 18 Years of Age) |  | (18 through 25 Years of Age)
fHbp Variant [For the third dose, serum was obtained approximately 1 month after vaccination.] |  | N [N=number of subjects with valid and determinate hSBA titers for the given strain.] | % (95% CI) [Exact 2-sided confidence interval (Clopper and Pearson) based upon the observed proportion of subjects.] | N | % (95% CI)
PMB3175 (A29) | Before Dose 1 | 169 | 11.2 (6.9, 17.0) | 160 | 23.8 (17.4, 31.1)
PMB3175 (A29) | Dose 3 | 176 | 98.9 (96.0, 99.9) | 162 | 98.8 (95.6, 99.9)
PMB3010 (A06) | Before Dose 1 | 178 | 7.9 (4.4, 12.8) | 166 | 10.8 (6.6, 16.6)
PMB3010 (A06) | Dose 3 | 179 | 97.8 (94.4, 99.4) | 164 | 89.0 (83.2, 93.4)
PMB3040 (A07) | Before Dose 1 | 170 | 37.6 (30.3, 45.4) | 165 | 55.8 (47.8, 63.5)
PMB3040 (A07) | Dose 3 | 178 | 96.1 (92.1, 98.4) | 165 | 95.2 (90.7, 97.9)
PMB824 (A12) | Before Dose 1 | 180 | 5.0 (2.3, 9.3) | 166 | 4.8 (2.1, 9.3)
PMB824 (A12) | Dose 3 | 180 | 76.1 (69.2, 82.1) | 165 | 66.7 (58.9, 73.8)
PMB1672 (A15) | Before Dose 1 | 170 | 15.9 (10.7, 22.3) | 159 | 30.2 (23.2, 38.0)
PMB1672 (A15) | Dose 3 | 166 | 86.7 (80.6, 91.5) | 159 | 89.9 (84.2, 94.1)
PMB1989 (A19) | Before Dose 1 | 174 | 5.7 (2.8, 10.3) | 158 | 23.4 (17.1, 30.8)
PMB1989 (A19) | Dose 3 | 173 | 91.9 (86.8, 95.5) | 163 | 94.5 (89.8, 97.4)
PMB1256 (B03) | Before Dose 1 | 183 | 2.2 (0.6, 5.5) | 164 | 5.5 (2.5, 10.2)
PMB1256 (B03) | Dose 3 | 181 | 92.3 (87.4, 95.7) | 161 | 84.5 (77.9, 89.7)
PMB866 (B09) | Before Dose 1 | 180 | 12.2 (7.8, 17.9) | 165 | 13.9 (9.0, 20.2)
PMB866 (B09) | Dose 3 | 182 | 85.7 (79.8, 90.5) | 162 | 72.2 (64.7, 79.0)
PMB431 (B15) | Before Dose 1 | 180 | 27.8 (21.4, 34.9) | 163 | 33.1 (26.0, 40.9)
PMB431 (B15) | Dose 3 | 183 | 97.3 (93.7, 99.1) | 163 | 95.7 (91.4, 98.3)
PMB648 (B16) | Before Dose 1 | 180 | 6.7 (3.5, 11.4) | 161 | 11.8 (7.3, 17.8)
PMB648 (B16) | Dose 3 | 180 | 83.9 (77.7, 88.9) | 159 | 72.3 (64.7, 79.1)
Abbreviations: CI=confidence interval; fHbp=factor H binding protein; hSBA=serum bactericidal assay using human complement; LLOQ=lower limit of quantitation.
Note: LLOQ = 1:16 for A06, A12, and A19; 1:8 for A07, A15, A29, B03, B09, B15, and B16.

In Study 1012, Trumenba was administered according to different schedules, including Group 1 (0, 1, and 6 months), Group 2 (0, 2, and 6 months) and Group 3 (0 and 6 months). The hSBA responses observed after the second dose in Groups 1, 2, and 3 and completion of the three-dose series in Group 1 and 2 are presented in Table 11.

Table 11: Percentages of European Subjects 11 through 18 Years of Age With a ≥4-Fold Increase in hSBA Titer and Composite Response [Per-schedule Evaluable populations. Dose 2 data include subjects who received two doses, irrespective of whether they received the third dose.] , [Study1012: NCT01299480.] (Study 1012)
 | Group 1 | Group 2 | Group 3
 | 3-Dose Schedule (0, 1, and 6 Months) [Group 1 (0, 1, and 6 months). The denominators ranged from 173 to 187 after Dose 2 and 178 to 188 after Dose 3, depending on the strain.] | 3-Dose Schedule (0, 2, and 6 Months) [Group 2 (0, 2, and 6 months). The denominators ranged from 229 to 240 after Dose 2 and 159 to 162 after Dose 3, depending on the strain.] | 2-Dose Schedule (0 and 6 Months) [Group 3 (0 and 6 months). The denominators ranged from 188 to 203 after Dose 2, depending on the strain.]
fHbp Variant [For the second and third doses, serum was obtained approximately 1 month after vaccination.] | % (95% CI) [Exact 2-sided confidence interval (Clopper and Pearson) based upon the observed proportion of subjects.] | % (95% CI) | % (95% CI)
≥4-Fold Increase
PMB80 (A22)
Dose 2 | 58.8 (51.4, 66.0) | 72.5 (66.4, 78.0) | 82.3 (76.3, 87.3)
Dose 3 | 77.6 (70.9, 83.4) | 87.7 (81.6, 92.3) | NA
PMB2001 (A56)
Dose 2 | 87.8 (82.2, 92.2) | 90.7 (86.2, 94.1) | 90.1 (85.1, 93.8)
Dose 3 | 91.2 (86.1, 94.9) | 93.8 (88.8, 97.0) | NA
PMB2948 (B24)
Dose 2 | 51.1 (43.6, 58.5) | 54.2 (47.7, 60.7) | 64.5 (57.4, 71.1)
Dose 3 | 74.1 (67.1, 80.2) | 78.3 (71.1, 84.4) | NA
PMB2707 (B44)
Dose 2 | 48.1 (40.7, 55.6) | 53.4 (46.8, 59.9) | 66.0 (58.9, 72.6)
Dose 3 | 80.9 (74.5, 86.2) | 78.6 (71.4, 84.7) | NA
Composite Response [Composite response = hSBA ≥LLOQ for all 4 primary meningococcal B strains.]
Before Dose 1 | 4.6 (2.0, 8.8) | 2.2 (0.7, 5.0) | 1.5 (0.3, 4.4)
Dose 2 | 52.0 (44.3, 59.7) | 52.0 (45.3, 58.6) | 72.9 (65.9, 79.1)
Dose 3 | 80.3 (73.7, 85.9) | 81.8 (74.9, 87.4) | NA
Abbreviations: CI=confidence interval; fHbp=factor H binding protein; hSBA=serum bactericidal assay using human complement; LLOQ=lower limit of quantitation; NA=not applicable.
Note: LLOQ = 1:16 for PMB80 (A22) and 1:8 for PMB2001 (A56), PMB2948 (B24), and PMB2707 (B44).
Note: The ≥4-fold increase is defined as follows: (1) For subjects with a baseline hSBA titer <1:4, a ≥4-fold increase was defined as an hSBA titer ≥1:16. (2) For subjects with a baseline hSBA titer ≥ LOD and < LLOQ, a response is defined as an hSBA titer ≥4 times the LLOQ. (3) For subjects with a baseline hSBA titer ≥ LLOQ, a response is defined as an hSBA titer ≥4 times the baseline titer.

14.2 Concomitant Vaccine Administration

Study B1971011 (Study 1011) evaluated the immunogenicity of concomitantly administered Trumenba and Human Papillomavirus Quadrivalent (Types 6, 11, 16, and 18) Vaccine, Recombinant (HPV4) (Merck & Co, Inc.). U.S. subjects 11 through 17 years of age were randomized into three groups: Group 1 received Trumenba and HPV4 (N=992), Group 2 received Trumenba and saline (N=990), and Group 3 received saline and HPV4 (N=501). All vaccines were administered according to a 0-, 2- and 6-month schedule. Immune responses were evaluated by comparisons of geometric mean titer [GMT] for each HPV type at 1 month after the third HPV4 vaccination (Group 1 vs. Group 3), and hSBA GMTs using two meningococcal serogroup B strains [variants A22 and B24] 1 month after the third Trumenba vaccination (Group 1 vs. Group 2). The noninferiority criteria for the comparisons of GMTs [lower limit of the 2-sided 95% confidence interval (CI) of the GMT ratio (Group 1/Group 3 for HPV and Group 1/Group 2 for meningococcal serogroup B strains) >0.67] were met for three HPV types (6, 11 and 16) and for the meningococcal serogroup B strains tested. For HPV-18, the lower bound of the 95% CI for the GMT ratio was 0.62 at 1 month after the third HPV4 vaccination

Study B1971015 (Study 1015) evaluated the immunogenicity of concomitantly administered Trumenba and Meningococcal (Serogroups A, C, Y and W-135) Polysaccharide Diphtheria Toxoid Conjugate Vaccine (MenACWY) (Sanofi Pasteur Inc.) and Tetanus Toxoid, Reduced Diphtheria Toxoid and Acellular Pertussis Vaccine Adsorbed (Tdap) (Sanofi Pasteur Ltd.) vaccines. U.S. subjects 10 through 12 years of age were randomized into three groups: Group 1 received Trumenba at 0, 2, and 6 months, and MenACWY and Tdap were coadministered with the first Trumenba dose (N=883). Group 2 received saline at 0, 2 and 6 months, and MenACWY and Tdap were coadministered with the first saline injection (N=870). Group 3 received Trumenba at 0, 2 and 6 months, and saline was coadministered with the first Trumenba dose (N=875). Immune responses were evaluated by comparisons of GMTs for each of the MenACWY and Tdap antigens 1 month after the first Trumenba vaccination, and hSBA GMTs using two meningococcal serogroup B strains [variants A22 and B24] 1 month after the third Trumenba vaccination. The noninferiority criteria for the comparisons of GMTs [lower limit of the 2-sided 95% CI of the GMT ratio (Group 1/Group 3 for meningococcal serogroup B strains and Group 1/Group 2 for MenACWY and Tdap) >0.67] were met for all antigens.

15 REFERENCES

1. Wang X, et al. Prevalence and genetic diversity of candidate vaccine antigens among invasive Neisseria meningitidis isolates in the U.S. Vaccine 2011; 29:4739–4744.

16 HOW SUPPLIED/STORAGE AND HANDLING

16.1 How Supplied

Trumenba is supplied in the following strengths and package configurations:

Prefilled Syringe, 1 Dose (10 per package) – NDC 0005-0100-10.

Prefilled Syringe, 1 Dose (5 per package) – NDC 0005-0100-05.

After shipping, Trumenba may arrive at temperatures between 2°C to 25°C (36°F to 77°F).

The tip cap and rubber plunger of the prefilled syringe are not made with natural rubber latex.

16.2 Storage and Handling

Upon receipt, store refrigerated at 2°C to 8°C (36°F to 46°F).

Store syringes in the refrigerator horizontally (laying flat on the shelf) to minimize the re-dispersion time.

Do not freeze. Discard if the vaccine has been frozen.

17 PATIENT COUNSELING INFORMATION

Prior to administration of this vaccine, the healthcare professional should inform the individual, parent, guardian, or other responsible adult of the following:

- The importance of completing the immunization series.
- Report any suspected adverse reactions to a healthcare professional.

Provide the Vaccine Information Statements, which are available free of charge at the Centers for Disease Control and Prevention (CDC) website (www.cdc.gov/vaccines).

U.S. Govt. License No. 3

LAB-0722-12.0

PRINCIPAL DISPLAY PANEL - 0.5 mL Syringe Label

NDC 0005-0100-01
Rx only

Meningococcal
Group B Vaccine

Trumenba®

One Dose (0.5 mL)
FOR IM USE ONLY
REFRIGERATE
DO NOT FREEZE
SHAKE VIGOROUSLY
Wyeth Pharm. LLC
US Govt. License No. 3

PRINCIPAL DISPLAY PANEL - 5 - 0.5 mL Syringe Carton

NDC 0005-0100-05

Meningococcal
Group B Vaccine

Trumenba®

For use in individuals
10 through 25 years of age

5 One-Dose (0.5 mL)
Prefilled Syringes

FOR INTRAMUSCULAR USE ONLY

Pfizer

Rx only

PRINCIPAL DISPLAY PANEL - 10 - 0.5 mL Syringe Carton

NDC 0005-0100-10

Meningococcal
Group B Vaccine

Trumenba®

For use in individuals
10 through 25 years of age

10 One-Dose (0.5 mL)
Prefilled Syringes

FOR INTRAMUSCULAR USE ONLY

Pfizer

Rx only